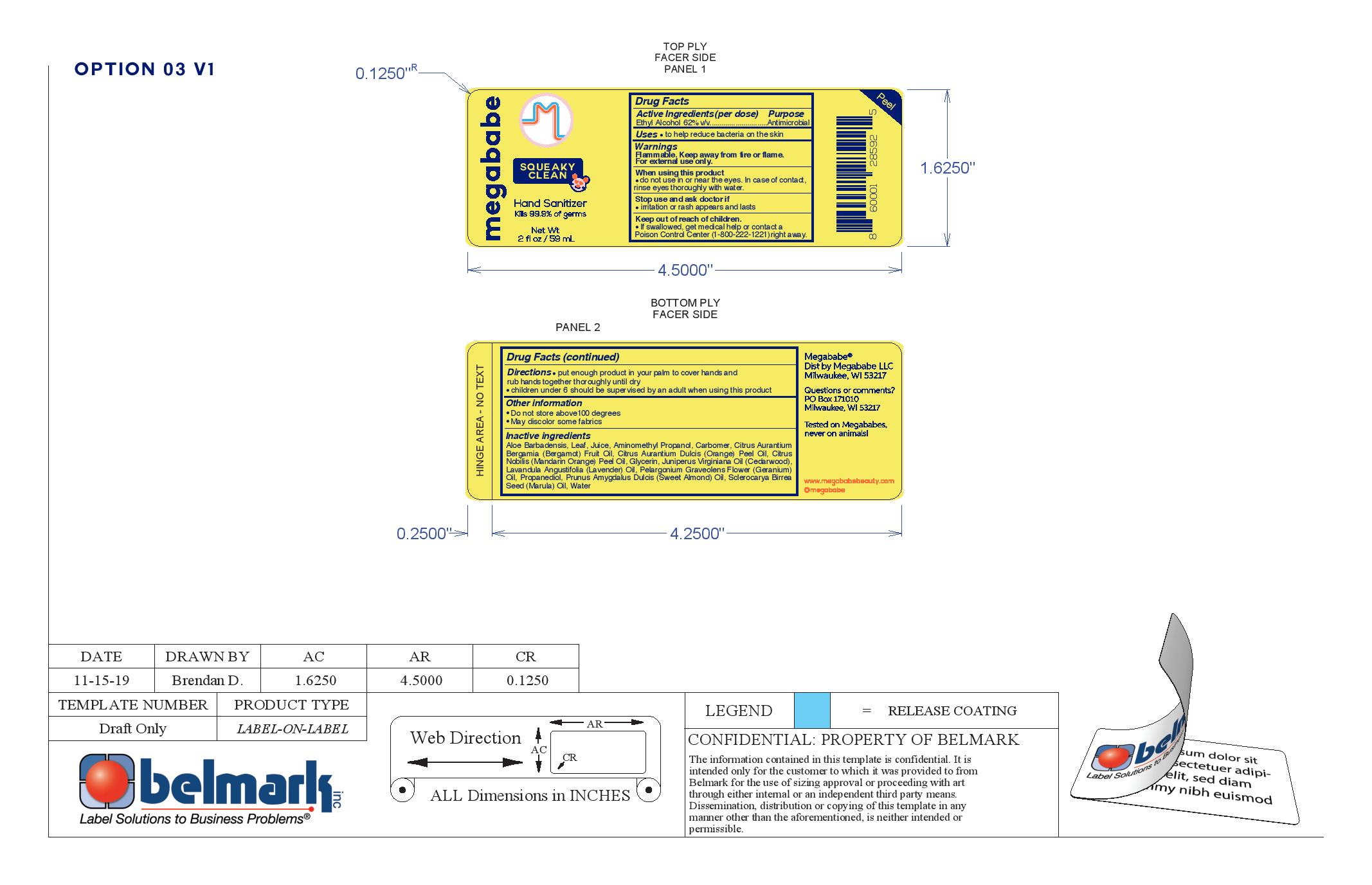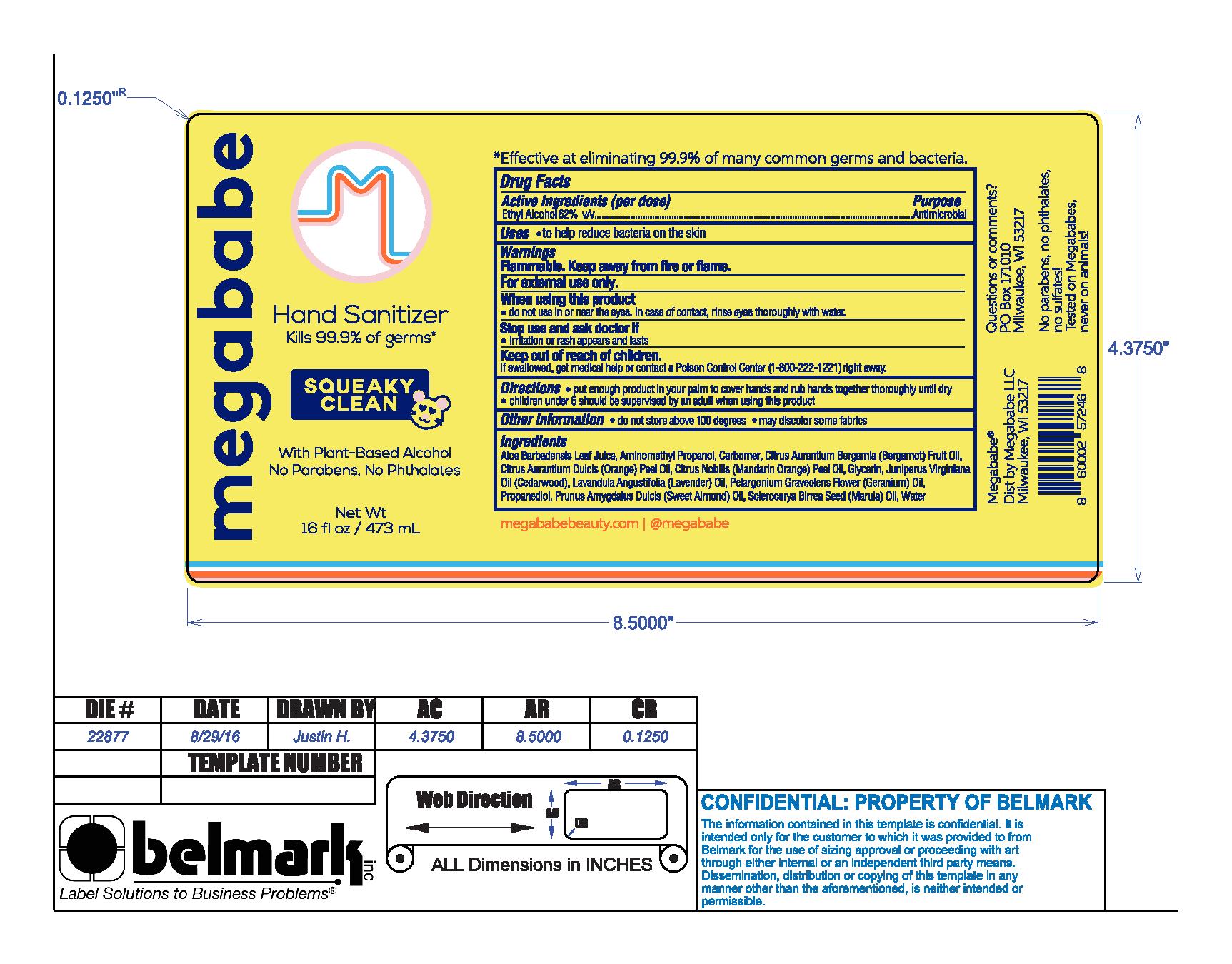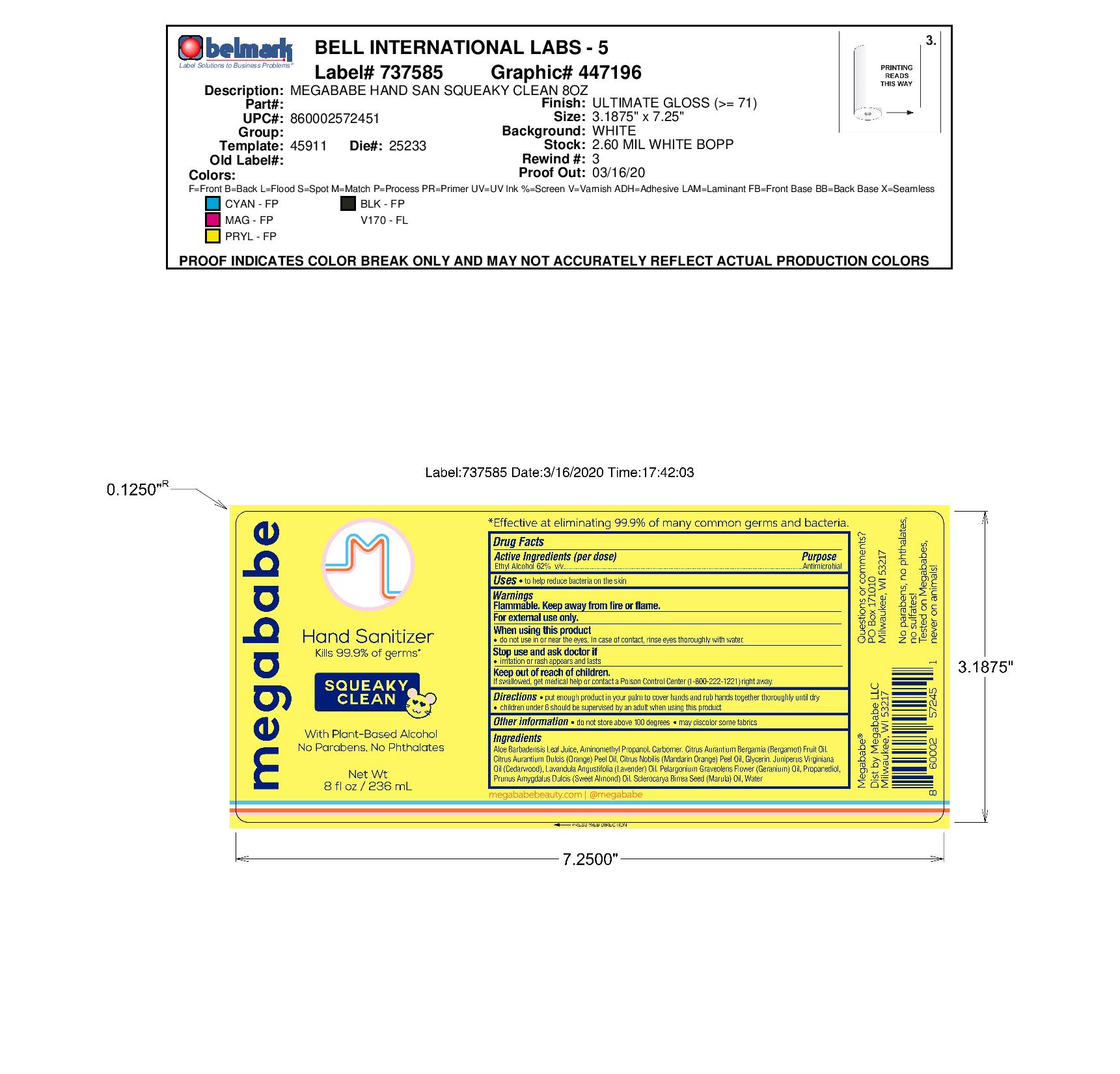 DRUG LABEL: Squeeky Clean
NDC: 76150-243 | Form: LIQUID
Manufacturer: Bell International Laboratories, Inc.
Category: otc | Type: HUMAN OTC DRUG LABEL
Date: 20200428

ACTIVE INGREDIENTS: ALCOHOL 62 mL/100 mL
INACTIVE INGREDIENTS: MANDARIN OIL; ALOE VERA LEAF; WATER; CARBOMER HOMOPOLYMER, UNSPECIFIED TYPE; PROPANEDIOL; GLYCERIN; ORANGE OIL; JUNIPERUS VIRGINIANA OIL; SCLEROCARYA BIRREA SEED OIL; LAVENDER OIL; PELARGONIUM GRAVEOLENS FLOWER OIL; ALMOND OIL; BERGAMOT OIL; AMINOMETHYLPROPANOL

Megababe Hand Sanitizer Gel

Active Ingredient

Ethyl Alcohol 62% v/v

Purpose

Antimicrobial

Uses

to help reduce bacteria on the skin

Warnings

Flammable. Keep away from fire or flame

For external use only

When using this product do not use in or near the eyes. In case of contact, rinse eyes thoroughly with water.

Stop use and ask doctor if irritation or rash appears and lasts

Keep out of reach of children. If swallowed, get medical help or contact a Poison Control Center (1-800-222-1221) right away.

Directions

put enough product in your palm to cover hands and rub them together thoroughly until dry. Children under 6 should be supervised by an adult when using this product.

Other Information

do not store above 100 degrees.

may discolor some fabrics

Ingredients

Aloe Barbadensis Leaf Juice, Aminomethyl Propanol, Carbomer, Citrus Aruantium Bergamia (Bergamot) Fruit Oil, Citrus Aurantium Dulcis (Orange) Peel Oil, Citrus Nobilis (Mandarin Orange) Peel Oil, Glycerin, Juniperus Virginiana Oil (Cedarwood), Lavandula Angustifolia (Lavender) Oil, Pelargonium Graveolens Flower (Geranium) Oil, Propanediol, Prunus Amygdalus Dulcis (sweet almond) Oil,, Sclerocarya Birrea Seed (Marula) Oil, Water